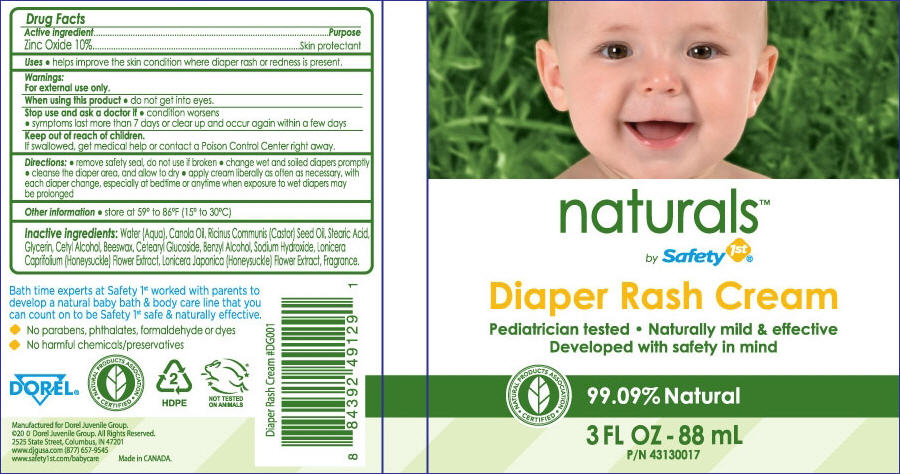 DRUG LABEL: Naturals by Safety 1st
NDC: 50428-3001 | Form: OINTMENT
Manufacturer: Dorel Juvenile Group
Category: otc | Type: HUMAN OTC DRUG LABEL
Date: 20121109

ACTIVE INGREDIENTS: ZINC OXIDE 8.8 g/88 mL
INACTIVE INGREDIENTS: WATER; CANOLA OIL; CASTOR OIL; STEARIC ACID; GLYCERIN; CETYL ALCOHOL; YELLOW WAX; CETEARYL GLUCOSIDE; BENZYL ALCOHOL; SODIUM HYDROXIDE; LONICERA CAPRIFOLIUM FLOWER; LONICERA JAPONICA FLOWER

Naturals™ by Safety 1st® Diaper Rash Cream

Active ingredient

Zinc Oxide 10%

Purpose

Skin Protectant

Uses

- Helps improve the skin condition where diaper rash or redness is present.

Warnings:

For external use only.

When using this product

- Do not get into eyes.

Stop use and ask a doctor if

- condition worsens
- symptoms last more than 7 days or clear up and occur again within a few days

Keep out of reach of children

If swallowed, get medical help or contact a Poison Control Center right away.

Directions

- remove safety seal, do not use if broken
- change wet and soiled diapers promptly
- cleanse the diaper area, and allow to dry
- apply cream liberally as often as necessary, with each diaper change, especially at bedtime or anytime when exposure to wet diapers may be prolonged

Other information

- store at 59° to 86° F (15° to 30° C)

Inactive ingredients

Water (Aqua), Canola Oil, Ricinus Communis (Castor) Seed Oil, Stearic Acid, Glycerin, Cetyl Alcohol, Beeswax, Cetearyl Glucoside, Benzyl Alcohol, Sodium Hydroxide, Lonicera Caprifoilum (Honeysuckle) Flower Extract, Lonicera Japanica (Honeysuckle) Flower Extract, Fragrance.

Principal Display Panel

naturals™ by Safety 1st® Diaper Rash Cream

Pediatrician tested · Naturally mild & effective

Developed with safety in mind

99.09% Natural

Bath time experts at Safety 1st worked with parents to develop a natural baby bath & body care line that you can count on to be Safety 1st safe & naturally effective.

- No parabens, phthalates, formaldehyde or dyes
- No harmful chemicals/preservatives

Manufactured for Dorel Juvenile Group.

©2010 Dorel Juvenile Group. All Rights Reserved.

2525 State Street, Columbus, IN 47201

www.djgusa.com (877)657-9545

www.safety1st.com/babycare

Made in CANADA

Tube Label